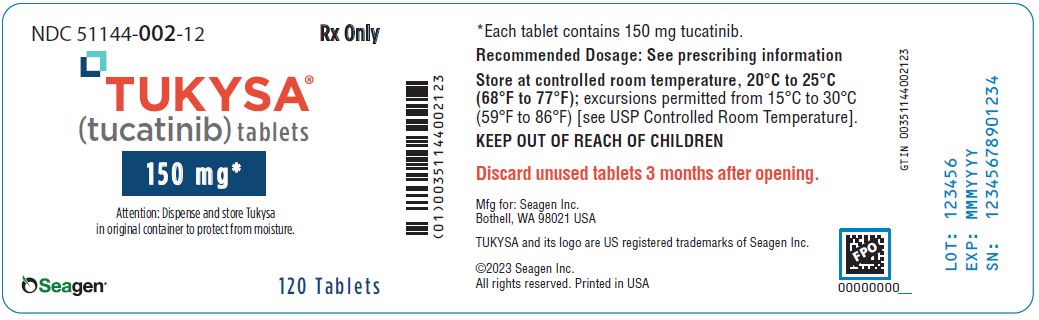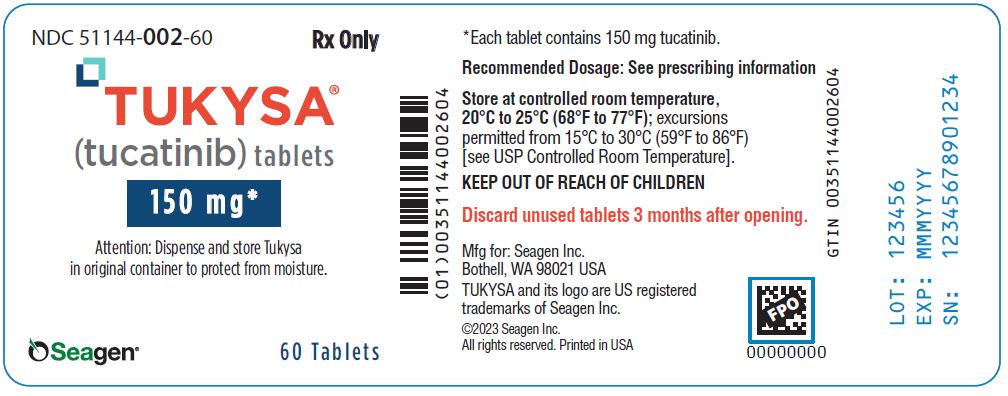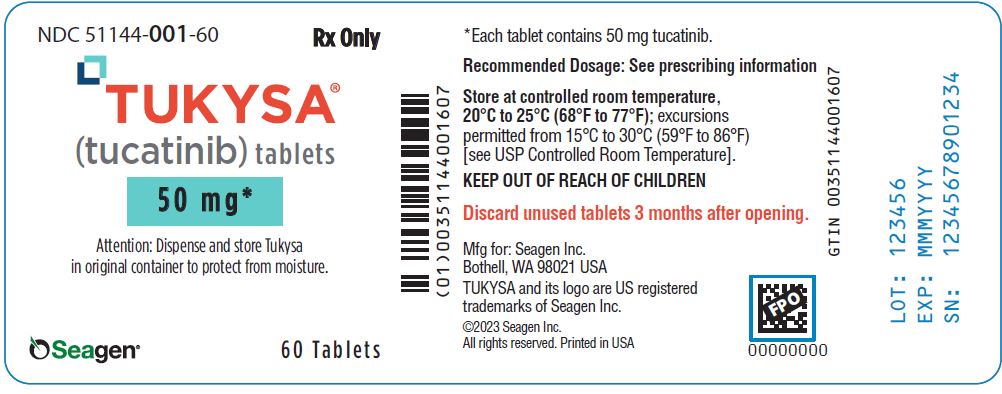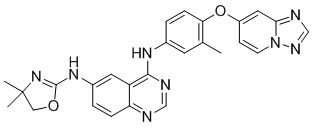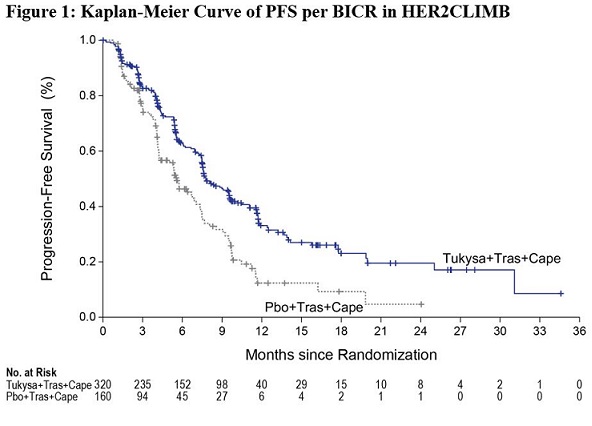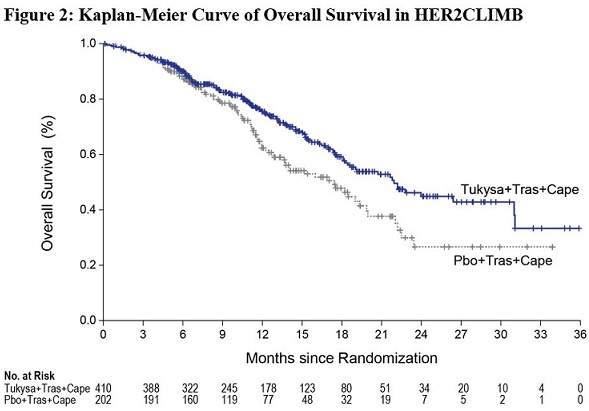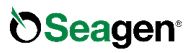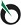 DRUG LABEL: TUKYSA
NDC: 51144-001 | Form: TABLET
Manufacturer: SEAGEN INC.
Category: prescription | Type: HUMAN PRESCRIPTION DRUG LABEL
Date: 20241104

ACTIVE INGREDIENTS: Tucatinib 50 mg/1 1
INACTIVE INGREDIENTS: Copovidone K25-31; Crospovidone (120 .Mu.M); Sodium Chloride; Potassium Chloride; Sodium Bicarbonate; Silicon Dioxide; Magnesium Stearate; Microcrystalline Cellulose 102; Polyvinyl Alcohol, Unspecified; Titanium Dioxide; Polyethylene Glycol, Unspecified; Talc; Ferric Oxide Yellow

HIGHLIGHTS OF PRESCRIBING INFORMATION

These highlights do not include all the information needed to use TUKYSA safely and effectively. See full prescribing information for TUKYSA.
TUKYSA® (tucatinib) tablets, for oral use
Initial U.S. Approval: 2020

1 INDICATIONS AND USAGE

TUKYSA is a kinase inhibitor indicated:

- in combination with trastuzumab and capecitabine for treatment of adult patients with advanced unresectable or metastatic HER2-positive breast cancer, including patients with brain metastases, who have received one or more prior anti-HER2-based regimens in the metastatic setting. (1.1)
- in combination with trastuzumab for the treatment of adult patients with RAS wild-type HER2-positive unresectable or metastatic colorectal cancer that has progressed following treatment with fluoropyrimidine-, oxaliplatin-, and irinotecan-based chemotherapy. (1.2)
  This indication is approved under accelerated approval based on tumor response rate and durability of response [see Clinical Studies (14.2)]. Continued approval for this indication may be contingent upon verification and description of clinical benefit in confirmatory trials.

RECENT MAJOR CHANGES

Indications and Usage (1.2) | 1/2023
Patient Selection (2.1) | 1/2023
Warnings and Precautions (5.1), (5.2) | 1/2023

2 DOSAGE AND ADMINISTRATION

- In patients with unresectable or metastatic colorectal cancer, confirm the presence of HER2 protein overexpression and RAS wild-type in tumor specimens prior to the initiation of TUKYSA (2.1)
- Recommended dosage: 300 mg taken orally twice daily with or without food. (2.1)
- For patients with severe hepatic impairment, the recommended dosage is 200 mg orally twice daily. (2.3, 8.7)

3 DOSAGE FORMS AND STRENGTHS

Tablets: 50 mg and 150 mg. (3)

4 CONTRAINDICATIONS

None. (4)

5 WARNINGS AND PRECAUTIONS

- Diarrhea: Severe diarrhea, including dehydration, acute kidney injury, and death, has been reported. Administer antidiarrheal treatment as clinically indicated. Interrupt dose, then dose reduce, or permanently discontinue TUKYSA based on severity. (2.2, 5.1)
- Hepatotoxicity: Severe hepatotoxicity has been reported on TUKYSA. Monitor ALT, AST and bilirubin prior to starting TUKYSA, every 3 weeks during treatment and as clinically indicated. Interrupt dose, then dose reduce, or permanently discontinue TUKYSA based on severity. (2.2, 5.2)
- Embryo-Fetal Toxicity: TUKYSA can cause fetal harm. Advise patients of potential risk to a fetus and to use effective contraception. (5.3, 8.1, 8.3)
  Also, refer to the Full Prescribing Information of trastuzumab and capecitabine for pregnancy and contraception information.

6 ADVERSE REACTIONS

- The most common adverse reactions (≥20%) with TUKYSA in combination with trastuzumab and capecitabine in patients with metastatic breast cancer are diarrhea, palmar-plantar erythrodysesthesia, nausea, hepatotoxicity, vomiting, stomatitis, decreased appetite, anemia, and rash. (6.1)
- The most common adverse reactions (≥20%) with TUKYSA in combination with trastuzumab in patients with unresectable or metastatic colorectal cancer are diarrhea, fatigue, rash, nausea, abdominal pain, infusion related reactions, and pyrexia.

To report SUSPECTED ADVERSE REACTIONS, contact Seagen at 1-855-4SEAGEN or FDA at 1-800-FDA-1088 or www.fda.gov/medwatch.

7 DRUG INTERACTIONS

- Strong CYP3A Inducers or Moderate CYP2C8 Inducers: Avoid concomitant use. (7.1)
- Strong CYP2C8 Inhibitors: Avoid concomitant use; reduce TUKYSA dose if concomitant use cannot be avoided. (2.4, 7.1)
- CYP3A Substrates: Avoid concomitant use with CYP3A substrates, where minimal concentration changes may lead to serious or life-threatening toxicities. (7.2)
- P-gp Substrates: Consider reducing the dose of P-gp substrates, where minimal concentration changes may lead to serious or life-threatening toxicities. (7.2)

8 USE IN SPECIFIC POPULATIONS

Lactation: Advise not to breastfeed. (8.2)

FULL PRESCRIBING INFORMATION

1 INDICATIONS AND USAGE

1.1 Metastatic Breast Cancer

TUKYSA is indicated in combination with trastuzumab and capecitabine for treatment of adult patients with advanced unresectable or metastatic HER2-positive breast cancer, including patients with brain metastases, who have received one or more prior anti-HER2-based regimens in the metastatic setting.

1.2 Unresectable or Metastatic Colorectal Cancer

TUKYSA is indicated in combination with trastuzumab for the treatment of adult patients with RAS wild-type, HER2-positive unresectable or metastatic colorectal cancer that has progressed following treatment with fluoropyrimidine-, oxaliplatin-, and irinotecan-based chemotherapy.

This indication is approved under accelerated approval based on tumor response rate and durability of response [see Clinical Studies (14.2)]. Continued approval for this indication may be contingent upon verification and description of clinical benefit in confirmatory trials.

2 DOSAGE AND ADMINISTRATION

2.1 Patient Selection

Select patients for treatment of unresectable or metastatic colorectal cancer with TUKYSA based on the presence of:

- HER2 overexpression or gene amplification [see Clinical Studies (14.2)]. FDA-approved tests for the detection of HER2 overexpression and gene amplification in patients with unresectable or metastatic colorectal cancer are not currently available, and
- RAS wild-type [see Clinical Studies (14.2)]. Information on FDA-approved tests for the detection of RAS mutations in patients with unresectable or metastatic colorectal cancer is available at http://www.fda.gov/CompanionDiagnostics.

2.2 Recommended Dosage

Metastatic Breast Cancer

The recommended dosage of TUKYSA is 300 mg taken orally twice daily in combination with trastuzumab and capecitabine until disease progression or unacceptable toxicity [see Clinical Studies (14.1)].

Unresectable or Metastatic Colorectal Cancer

The recommended dosage of TUKYSA is 300 mg taken orally twice daily in combination with trastuzumab until disease progression or unacceptable toxicity [see Clinical Studies (14.2)].

Advise patients to swallow TUKYSA tablets whole and not to chew, crush, or split prior to swallowing. Advise patients not to ingest tablet if it is broken, cracked, or not otherwise intact.

Advise patients to take TUKYSA approximately 12 hours apart and at the same time each day with or without a meal.

If the patient vomits or misses a dose of TUKYSA, instruct the patient to take the next dose at its usual scheduled time.

When given in combination with TUKYSA, the recommended dosage of capecitabine is 1000 mg/m^2 orally twice daily taken within 30 minutes after a meal. TUKYSA and capecitabine can be taken at the same time. Refer to the Full Prescribing Information for trastuzumab and capecitabine for additional information.

2.3 Dosage Modifications for Adverse Reactions

The recommended TUKYSA dose reductions and dosage modifications for adverse reactions are provided in Tables 1 and 2. Refer to the Full Prescribing Information for trastuzumab and capecitabine for information about dosage modifications for these drugs.

Table 1: Recommended TUKYSA Dose Reductions for Adverse Reactions
Dose Reduction | Recommended TUKYSA Dosage
First | 250 mg orally twice daily
Second | 200 mg orally twice daily
Third | 150 mg orally twice daily

Permanently discontinue TUKYSA in patients unable to tolerate 150 mg orally twice daily.

Table 2: Recommended TUKYSA Dosage Modifications for Adverse Reactions
Adverse Reaction [Grades based on National Cancer Institute Common Terminology Criteria for Adverse Events Version 4.03] | Severity | TUKYSA Dosage Modification
Diarrhea [see Warnings and Precautions (5.1)] | Grade 3 without anti-diarrheal treatment | Initiate or intensify appropriate medical therapy. Hold TUKYSA until recovery to ≤ Grade 1, then resume TUKYSA at the same dose level.
Diarrhea [see Warnings and Precautions (5.1)] | Grade 3 with anti-diarrheal treatment | Initiate or intensify appropriate medical therapy. Hold TUKYSA until recovery to ≤ Grade 1, then resume TUKYSA at the next lower dose level.
Diarrhea [see Warnings and Precautions (5.1)] | Grade 4 | Permanently discontinue TUKYSA.
Hepatotoxicity [Abbreviations: ULN = upper limit of normal; ALT = alanine aminotransferase; AST = aspartate aminotransferase] [see Warnings and Precautions (5.2)] | Grade 2 bilirubin (>1.5 to 3 × ULN) | Hold TUKYSA until recovery to ≤ Grade 1, then resume TUKYSA at the same dose level.
Hepatotoxicity [Abbreviations: ULN = upper limit of normal; ALT = alanine aminotransferase; AST = aspartate aminotransferase] [see Warnings and Precautions (5.2)] | Grade 3 ALT or AST (> 5 to 20 × ULN) OR Grade 3 bilirubin (> 3 to 10 × ULN) | Hold TUKYSA until recovery to ≤ Grade 1, then resume TUKYSA at the next lower dose level.
Hepatotoxicity [Abbreviations: ULN = upper limit of normal; ALT = alanine aminotransferase; AST = aspartate aminotransferase] [see Warnings and Precautions (5.2)] | Grade 4 ALT or AST (> 20 × ULN) OR Grade 4 bilirubin (> 10 × ULN) | Permanently discontinue TUKYSA.
Hepatotoxicity [Abbreviations: ULN = upper limit of normal; ALT = alanine aminotransferase; AST = aspartate aminotransferase] [see Warnings and Precautions (5.2)] | ALT or AST > 3 × ULN AND Bilirubin > 2 × ULN | Permanently discontinue TUKYSA.
Other adverse reactions [see Adverse Reactions (6.1)] | Grade 3 | Hold TUKYSA until recovery to ≤ Grade 1, then resume TUKYSA at the next lower dose level.
Other adverse reactions [see Adverse Reactions (6.1)] | Grade 4 | Permanently discontinue TUKYSA.

2.4 Dosage Modifications for Severe Hepatic Impairment

For patients with severe hepatic impairment (Child-Pugh C), reduce the recommended dosage to 200 mg orally twice daily [see Use in Specific Populations (8.7), Clinical Pharmacology (12.3)].

2.5 Dosage Modifications for Concomitant Use with Strong CYP2C8 Inhibitors

Avoid concomitant use of strong CYP2C8 inhibitors with TUKYSA. If concomitant use with a strong CYP2C8 inhibitor cannot be avoided, reduce the recommended dosage to 100 mg orally twice daily. After discontinuation of the strong CYP2C8 inhibitor for 3 elimination half-lives, resume the TUKYSA dose that was taken prior to initiating the inhibitor [see Drug Interactions (7.1), Clinical Pharmacology (12.3)].

3 DOSAGE FORMS AND STRENGTHS

Tablets:

- 50 mg: round, yellow, film-coated, debossed with “TUC” on one side and “50” on the other side.
- 150 mg: oval-shaped, yellow, film-coated, debossed with “TUC” on one side and “150” on the other side.

4 CONTRAINDICATIONS

None.

5 WARNINGS AND PRECAUTIONS

5.1 Diarrhea

TUKYSA can cause severe diarrhea including dehydration, hypotension, acute kidney injury, and death [see Adverse Reactions (6.1)].

If diarrhea occurs, administer antidiarrheal treatment as clinically indicated. Perform diagnostic tests as clinically indicated to exclude other causes of diarrhea. Based on the severity of the diarrhea, interrupt dose, then dose reduce or permanently discontinue TUKYSA [see Dosage and Administration (2.2)].

TUKYSA with trastuzumab and capecitabine

In HER2CLIMB, 81% of patients who received TUKYSA experienced diarrhea, including 0.5% with Grade 4 diarrhea and 12% with Grade 3 diarrhea. Both patients who developed Grade 4 diarrhea subsequently died, with diarrhea as a contributor to death. The median time to onset of the first episode of diarrhea was 12 days and the median time to resolution was 8 days. Diarrhea led to dose reductions of TUKYSA in 6% of patients and discontinuation of TUKYSA in 1% of patients. Prophylactic use of antidiarrheal treatment was not required on HER2CLIMB.

TUKYSA with trastuzumab

In MOUNTAINEER, diarrhea occurred in 64% of patients, including Grade 3 (3.5%), Grade 2 (10%), and Grade 1 (50%).

5.2 Hepatotoxicity

TUKYSA can cause severe hepatotoxicity [see Adverse Reactions (6.1)].

Monitor ALT, AST, and bilirubin prior to starting TUKYSA, every 3 weeks during treatment, and as clinically indicated. Based on the severity of hepatotoxicity, interrupt dose, then dose reduce or permanently discontinue TUKYSA [see Dosage and Administration (2.2)].

TUKYSA with trastuzumab and capecitabine

In HER2CLIMB, 8% of patients who received TUKYSA had an ALT increase > 5 × ULN, 6% had an AST increase > 5 × ULN, and 1.5% had a bilirubin increase > 3 × ULN (Grade ≥3). Hepatotoxicity led to dose reduction of TUKYSA in 8% of patients and discontinuation of TUKYSA in 1.5% of patients.

TUKYSA with trastuzumab

In MOUNTAINEER, 6% of patients had a bilirubin increase > 3 × ULN (Grade ≥3), 6% had an AST increase > 5 × ULN, and 4.7% had an ALT increase > 5 × ULN. Hepatotoxicity led to dose reduction of TUKYSA in 3.5% of patients and discontinuation of TUKYSA in 2.3% of patients.

5.3 Embryo-Fetal Toxicity

Based on findings from animal studies and its mechanism of action, TUKYSA can cause fetal harm when administered to a pregnant woman. In animal reproduction studies, administration of tucatinib to pregnant rats and rabbits during organogenesis caused embryo-fetal mortality, reduced fetal weight and fetal abnormalities at maternal exposures ≥ 1.3 times the human exposure (AUC) at the recommended dose.

Advise pregnant women and females of reproductive potential of the potential risk to a fetus. Advise females of reproductive potential to use effective contraception during treatment with TUKYSA and for 1 week after the last dose. Advise male patients with female partners of reproductive potential to use effective contraception during treatment with TUKYSA and for 1 week after the last dose [see Use in Specific Populations (8.1, 8.3)].

TUKYSA is used in combination with trastuzumab and capecitabine. Refer to the Full Prescribing Information of trastuzumab and capecitabine for pregnancy and contraception information.

6 ADVERSE REACTIONS

The following clinically significant adverse reactions are described elsewhere in the labeling:

- Diarrhea [see Warnings and Precautions (5.1)]
- Hepatotoxicity [see Warnings and Precautions (5.2)]

6.1 Clinical Trials Experience

Because clinical trials are conducted under widely varying conditions, adverse reaction rates observed in the clinical trials of a drug cannot be directly compared to rates in the clinical trials of another drug and may not reflect the rates observed in practice.

HER2-Positive Metastatic Breast Cancer

The safety of TUKYSA in combination with trastuzumab and capecitabine was evaluated in HER2CLIMB [see Clinical Studies (14)]. Patients received either TUKYSA 300 mg twice daily plus trastuzumab or a non-US approved trastuzumab product, and capecitabine (n=404) or placebo plus trastuzumab or a non-US approved trastuzumab product and capecitabine (n=197). The median duration of treatment was 5.8 months (range: 3 days, 2.9 years) for the TUKYSA arm.

Serious adverse reactions occurred in 26% of patients who received TUKYSA. Serious adverse reactions in ≥ 2% of patients who received TUKYSA were diarrhea (4%), vomiting (2.5%), nausea (2%), abdominal pain (2%), and seizure (2%). Fatal adverse reactions occurred in 2% of patients who received TUKYSA including sudden death, sepsis, dehydration, and cardiogenic shock.

Adverse reactions leading to treatment discontinuation occurred in 6% of patients who received TUKYSA. Adverse reactions leading to treatment discontinuation of TUKYSA in ≥1% of patients were hepatotoxicity (1.5%) and diarrhea (1%).

Adverse reactions leading to dose reduction occurred in 21% of patients who received TUKYSA. Adverse reactions leading to dose reduction of TUKYSA in ≥2% of patients were hepatotoxicity (8%) and diarrhea (6%).

The most common adverse reactions in patients who received TUKYSA (≥20%) were diarrhea, palmar-plantar erythrodysesthesia, nausea, hepatotoxicity, vomiting, stomatitis, decreased appetite, anemia, and rash.

Table 3 summarizes the adverse reactions in HER2CLIMB.

Table 3: Adverse Reactions (≥10%) in Patients Who Received TUKYSA and with a Difference Between Arms of ≥ 5% Compared to Placebo in HER2CLIMB (All Grades)
Adverse Reaction | TUKYSA + Trastuzumab + Capecitabine; N = 404 |  |  | Placebo + Trastuzumab + Capecitabine; N = 197
Adverse Reaction | All Grades; % | Grade 3; % | Grade 4; % | All Grades; % | Grade 3; % | Grade 4; %
Gastrointestinal disorders
Diarrhea | 81 | 12 | 0.5 | 53 | 9 | 0
Nausea | 58 | 3.7 | 0 | 44 | 3 | 0
Vomiting | 36 | 3 | 0 | 25 | 3.6 | 0
Stomatitis [Stomatitis includes stomatitis, oropharyngeal pain, oropharyngeal discomfort, mouth ulceration, oral pain, lip ulceration, glossodynia, tongue blistering, lip blister, oral dysesthesia, tongue ulceration, and aphthous ulcer] | 32 | 2.5 | 0 | 21 | 0.5 | 0
Skin and subcutaneous tissue disorders
Palmar-plantar erythrodysesthesia syndrome | 63 | 13 | 0 | 53 | 9 | 0
Rash [Rash includes rash maculo-papular, rash, dermatitis acneiform, erythema, rash macular, rash papular, rash pustular, rash pruritic, rash erythematous, skin exfoliation, urticaria, dermatitis allergic, palmar erythema, plantar erythema, skin toxicity, and dermatitis] | 20 | 0.7 | 0 | 15 | 0.5 | 0
Hepatobiliary disorders
Hepatotoxicity [Hepatotoxicity includes hyperbilirubinemia, blood bilirubin increased, bilirubin conjugated increased, alanine aminotransferase increased, transaminases increased, hepatotoxicity, aspartate aminotransferase increased, liver function test increased, liver injury, and hepatocellular injury] | 42 | 9 | 0.2 | 24 | 3.6 | 0
Metabolism and nutrition disorders
Decreased appetite | 25 | 0.5 | 0 | 20 | 0 | 0
Blood and lymphatic system disorders
Anemia [Anemia includes anemia, hemoglobin decreased, and normocytic anemia] | 21 | 3.7 | 0 | 13 | 2.5 | 0
Musculoskeletal and connective tissue disorders
Arthralgia | 15 | 0.5 | 0 | 4.6 | 0.5 | 0
Investigations
Creatinine increased [Due to inhibition of renal tubular transport of creatinine without affecting glomerular function] | 14 | 0 | 0 | 1.5 | 0 | 0
Weight decreased | 13 | 1 | 0 | 6 | 0.5 | 0
Nervous System Disorders
Peripheral neuropathy [Peripheral neuropathy includes peripheral sensory neuropathy, neuropathy peripheral, peripheral motor neuropathy, and peripheral sensorimotor neuropathy] | 13 | 0.5 | 0 | 7 | 1 | 0
Respiratory, thoracic and mediastinal disorders
Epistaxis | 12 | 0 | 0 | 5 | 0 | 0

Table 4: Laboratory Abnormalities (≥20%) Worsening from Baseline in Patients Who Received TUKYSA and with a Difference of ≥5% Compared to Placebo in HER2CLIMB
Laboratory Abnormality | TUKYSA + Trastuzumab +Capecitabine [The denominator used to calculate the rate varied from 351 to 400 in the TUKYSA arm and 173 to 197 in the control arm based on the number of patients with a baseline value and at least one post-treatment value. Grading was based on NCI-CTCAE v.4.03 for laboratory abnormalities, except for increased creatinine which only includes patients with a creatinine increase based on the upper limit of normal definition for grade 1 events (NCI CTCAE v5.0).] |  | Placebo + Trastuzumab +Capecitabine
Laboratory Abnormality | All Grades; % | Grades ≥3; % | All Grades; % | Grades ≥3; %
Hematology
Decreased hemoglobin | 59 | 3.3 | 51 | 1.5
Chemistry
Decreased phosphate | 57 | 8 | 45 | 7
Increased bilirubin | 47 | 1.5 | 30 | 3.1
Increased ALT | 46 | 8 | 27 | 0.5
Increased AST | 43 | 6 | 25 | 1
Decreased magnesium | 40 | 0.8 | 25 | 0.5
Decreased potassium [Laboratory criteria for Grade 1 is identical to laboratory criteria for Grade 2.] | 36 | 6 | 31 | 5
Increased creatinine [Due to inhibition of renal tubular transport of creatinine without affecting glomerular function.] | 33 | 0 | 6 | 0
Decreased sodium [There is no definition for Grade 2 in CTCAE v.4.03.] | 28 | 2.5 | 23 | 2
Increased alkaline phosphatase | 26 | 0.5 | 17 | 0

Increased Creatinine

The mean increase in serum creatinine was 32% within the first 21 days of treatment with TUKYSA. The serum creatinine increases persisted throughout treatment and were reversible upon treatment completion. Consider alternative markers of renal function if persistent elevations in serum creatinine are observed [see Clinical Pharmacology (12.3)].

RAS Wild-Type, HER2-Positive Unresectable or Metastatic Colorectal Cancer

The safety of TUKYSA in combination with trastuzumab or a non-US approved trastuzumab product was evaluated in 86 patients enrolled in MOUNTAINEER with unresectable or metastatic colorectal cancer [see Clinical Studies (14.2)]. The median duration of exposure to TUKYSA was 6.9 months (range 0.7, 49.3).

Serious adverse reactions occurred in 22% of patients. Serious adverse reactions that occurred in ≥ 2% of patients were intestinal obstruction (7%), urinary tract infection (3.5%), pneumonia (2.3%), abdominal pain (2.3%) and rectal perforation (2.3%).

Permanent discontinuation of TUKYSA due to an adverse reaction occurred in 6% of patients. The adverse reaction which resulted in permanent discontinuation of TUKYSA in ≥2% of patients was increased ALT (2.3%). Dosage interruptions of TUKYSA due to an adverse reaction occurred in 23% of patients. Adverse reactions which required dosage interruption in ≥3% of patients were increased ALT (3.5%) and diarrhea (3.5%). Dose reductions of TUKYSA due to an adverse reaction occurred in 9% of patients. Adverse reactions which required dose reductions in ≥2% of patients were increased ALT (2.3%) and diarrhea (2.3%).

The most common adverse reactions reported in ≥ 20% of patients treated with TUKYSA and trastuzumab were diarrhea, fatigue, rash, nausea, abdominal pain, infusion related reactions, and pyrexia. The most common laboratory abnormalities reported in ≥ 20% of patients were increased creatinine, increased glucose, increased ALT, decreased hemoglobin, increased AST, increased bilirubin, increased alkaline phosphatase, decreased lymphocytes, decreased albumin, decreased leukocytes, and decreased sodium.

Table 5 summarizes the adverse reactions in MOUNTAINEER.

Table 5: Adverse Reactions (≥10%) in Patients with Unresectable or Metastatic Colorectal Cancer (MOUNTAINEER)
Adverse Reaction | TUKYSA + Trastuzumab; N= 86 [Includes 1 patient who only received trastuzumab.]
Adverse Reaction | All Grades; % | Grade 3; %
Gastrointestinal disorders
Diarrhea | 64 | 3.5
Nausea | 35 | 0
Vomiting | 16 | 0
Abdominal pain [Abdominal pain includes abdominal discomfort, abdominal pain, and abdominal pain upper.] | 21 | 2.3
Constipation | 14 | 1.2
General disorders
Fatigue | 44 | 2.3
Pyrexia | 20 | 0
Chills | 19 | 1.2
Skin and subcutaneous disorders
Rash [Rash includes acne, dermatitis acneiform, dermatitis contact, erythema, erythema multiforme, rash, rash macular, rash maculo-papular, rash papular, rash pustular, skin exfoliation, and urticaria.] | 37 | 0
Injury, poisoning, and procedural complications
Infusion related reaction | 21 | 0
Metabolism and nutrition disorders
Decreased appetite | 19 | 0
Blood and lymphatic system disorders
Anemia | 10 | 0
Vascular disorders
Hypertension | 17 | 7
Musculoskeletal and connective tissue disorders
Back pain | 17 | 2.3
Arthralgia | 16 | 1.2
Myalgia | 13 | 0
Respiratory, thoracic and mediastinal disorders
Cough | 16 | 0
Dyspnea | 14 | 0
Psychiatric disorders
Anxiety | 10 | 0

Other adverse reactions (<10%) include epistaxis (7%), weight decreased (7%), oropharyngeal pain (5%), oral dysesthesia (1%), and stomatitis (1%).

Table 6: Laboratory Abnormalities (≥15%) Worsening from Baseline in Patients with Unresectable or Metastatic Colorectal Cancer (MOUNTAINEER)
Laboratory Abnormality | TUKYSA + Trastuzumab; N=85 [Number of patients with both baseline and post-baseline results for each test]
Laboratory Abnormality | All Grades; % | Grade 3; % | Grade 4; %
Hematology
Decreased hemoglobin | 46 | 3.5 | 0
Decreased lymphocytes | 39 | 12 | 0
Decreased leukocytes | 22 | 0 | 0
Decreased platelets | 15 | 0 | 0
Chemistry
Increased creatinine [NCI CTCAE v5.0 was used for creatinine increased. NCI CTCAE v4.03 was used for all other laboratory parameters.] , [Due to inhibition of renal tubular transport of creatinine without affecting glomerular function] | 58 | 0 | 0
Increased glucose | 56 | 2.4 | 0
Increased ALT | 46 | 2.4 | 2.4
Increased AST | 33 | 2.4 | 3.5
Increased bilirubin | 28 | 3.5 | 2.4
Increased alkaline phosphatase | 25 | 1.2 | 0
Decreased albumin | 24 | 1.2 | 0
Decreased sodium | 20 | 6 | 0
Decreased potassium | 16 | 1.2 | 0

Increased Creatinine

The mean increase in serum creatinine was 32% within the first 21 days of treatment with TUKYSA. The serum creatinine increases persisted throughout treatment and were reversible in 87% of patients with values outside normal lab limits upon treatment completion. Consider alternative markers of renal function if persistent elevations in serum creatinine are observed [see Clinical Pharmacology (12.3)].

7 DRUG INTERACTIONS

7.1 Effects of Other Drugs on TUKYSA

Table 7 summarizes the effect of other drugs on TUKYSA.

Table 7: Drug Interactions that Affect TUKYSA
Strong CYP3A Inducers or Moderate CYP2C8 Inducers
Clinical Impact | Concomitant use of TUKYSA with a strong CYP3A or moderate CYP2C8 inducer decreased tucatinib plasma concentrations [see Clinical Pharmacology (12.3)], which may reduce TUKYSA activity.
Management | Avoid concomitant use of TUKYSA with a strong CYP3A inducer or a moderate CYP2C8 inducer.
Strong or Moderate CYP2C8 Inhibitors
Clinical Impact | Concomitant use of TUKYSA with a strong CYP2C8 inhibitor increased tucatinib plasma concentrations [see Clinical Pharmacology (12.3)], which may increase the risk of TUKYSA toxicity.
Management | Avoid concomitant use of TUKYSA with a strong CYP2C8 inhibitor. Increase monitoring for TUKYSA toxicity with moderate CYP2C8 inhibitors.

7.2 Effects of TUKYSA on Other Drugs

Table 8 summarizes the effect of TUKYSA on other drugs.

Table 8: TUKYSA Drug Interactions that Affect Other Drugs
CYP3A Substrates
Clinical Impact | Concomitant use of TUKYSA with a CYP3A substrate increased the plasma concentrations of CYP3A substrate [see Clinical Pharmacology (12.3)], which may increase the toxicity associated with a CYP3A substrate.
Management | Avoid concomitant use of TUKYSA with CYP3A substrates, where minimal concentration changes may lead to serious or life-threatening toxicities. If concomitant use is unavoidable, decrease the CYP3A substrate dosage in accordance with approved product labeling.
P-glycoprotein (P-gp) Substrates
Clinical Impact | Concomitant use of TUKYSA with a P-gp substrate increased the plasma concentrations of P-gp substrate [see Clinical Pharmacology (12.3)], which may increase the toxicity associated with a P-gp substrate.
Management | Consider reducing the dosage of P-gp substrates, where minimal concentration changes may lead to serious or life-threatening toxicities.

8 USE IN SPECIFIC POPULATIONS

8.1 Pregnancy

Risk Summary

TUKYSA is used in combination with trastuzumab and capecitabine. Refer to the Full Prescribing Information of trastuzumab and capecitabine for pregnancy information.

Based on findings in animals and its mechanism of action, TUKYSA can cause fetal harm when administered to a pregnant woman [see Clinical Pharmacology (12.1)]. There are no available human data on TUKYSA use in pregnant women to inform a drug-associated risk. In animal reproduction studies, administration of tucatinib to pregnant rats and rabbits during organogenesis resulted in embryo-fetal mortality, reduced fetal weight and fetal abnormalities at maternal exposures ≥ 1.3 times the human exposure (AUC) at the recommended dose (see Data). Advise pregnant women and females of reproductive potential of the potential risk to the fetus.

The background risk of major birth defects and miscarriage for the indicated population is unknown. In the U.S. general population, the estimated background risk of major birth defects and miscarriage in clinically recognized pregnancies is 2%-4% and 15%-20%, respectively.

Data

Animal Data

In pilot embryo-fetal development studies, pregnant rats and rabbits received oral doses of tucatinib up to 150 mg/kg/day during the period of organogenesis.

In rats, oral administration of tucatinib resulted in maternal toxicity (body weight loss, reduced body weight gain, low food consumption) at doses ≥ 90 mg/kg/day. Fetal effects included reduced number of live fetuses, decreased fetal weight, and fetal abnormalities (increase in skeletal variations, incomplete ossification) at ≥ 90 mg/kg/day (approximately 3.5 times the human exposure at the recommended dose based on AUC).

In rabbits, oral administration of tucatinib resulted in increased resorptions, decreased percentages of live fetuses, and skeletal, visceral, and external malformations in fetuses at doses ≥ 90 mg/kg/day (1.3 times the human exposure at the recommended dose based on AUC). Fetal abnormalities included domed head, brain dilation, incomplete ossification of frontal and parietal bones, and a hole in the parietal bone.

8.2 Lactation

Risk Summary

TUKYSA is used in combination with trastuzumab and capecitabine. Refer to the Full Prescribing Information of trastuzumab and capecitabine for lactation information.

There are no data on the presence of tucatinib or its metabolites in human or animal milk or its effects on the breastfed child or on milk production. Because of the potential for serious adverse reactions in a breastfed child, advise women not to breastfeed during treatment with TUKYSA and for 1 week after the last dose.

8.3 Females and Males of Reproductive Potential

TUKYSA can cause fetal harm when administered to a pregnant woman [see Use in Specific Populations (8.1)]. TUKYSA is used in combination with trastuzumab and capecitabine. Refer to the Full Prescribing Information of trastuzumab and capecitabine for contraception and infertility information.

Pregnancy Testing

Verify the pregnancy status of females of reproductive potential prior to initiating treatment with TUKYSA.

Contraception

Females

Advise females of reproductive potential to use effective contraception during treatment with TUKYSA and for 1 week after the last dose.

Males

Advise male patients with female partners of reproductive potential to use effective contraception during treatment with TUKYSA and for 1 week after the last dose.

Infertility

Based on findings from animal studies, TUKYSA may impair male and female fertility [see Nonclinical Toxicology (13.1)].

8.4 Pediatric Use

The safety and effectiveness of TUKYSA in pediatric patients have not been established.

8.5 Geriatric Use

In HER2CLIMB, 82 patients who received TUKYSA were ≥ 65 years, of whom 8 patients were ≥ 75 years. The incidence of serious adverse reactions in those receiving TUKYSA was 34% in patients ≥ 65 years compared to 24% in patients <65 years. The most frequent serious adverse reactions in patients ≥65 years who received TUKYSA were diarrhea (9%), vomiting (6%), and nausea (5%). There were no observed overall differences in the effectiveness of TUKYSA in patients ≥ 65 years compared to younger patients. There were too few patients ≥75 years to assess differences in effectiveness or safety.

In MOUNTAINEER, 12 patients were ≥65 years of age. There were too few patients ≥65 years to assess differences in effectiveness or safety.

8.6 Renal Impairment

The use of TUKYSA in combination with capecitabine and trastuzumab is not recommended in patients with severe renal impairment (creatinine clearance [CLcr]: < 30 mL/min estimated by Cockcroft-Gault Equation), because capecitabine is contraindicated in patients with severe renal impairment. Refer to the Full Prescribing Information of capecitabine for additional information in severe renal impairment.

No dose adjustment is recommended for patients with mild or moderate renal impairment (CLcr: 30 to 89 mL/min).

8.7 Hepatic Impairment

Tucatinib exposure is increased in patients with severe hepatic impairment (Child-Pugh C). Reduce the dose of TUKYSA for patients with severe (Child-Pugh C) hepatic impairment [see Dosage and Administration (2.3), Clinical Pharmacology (12.3)].

No dose adjustment for TUKYSA is required for patients with mild (Child-Pugh A) or moderate (Child-Pugh B) hepatic impairment.

11 DESCRIPTION

Tucatinib is a kinase inhibitor. The chemical name is (N4-(4-([1,2,4]triazolo[1,5-a]pyridin-7-yloxy)-3-methylphenyl)-N6-(4,4-dimethyl-4,5-dihydrooxazol-2-yl)quinazoline-4,6-diamine. The molecular formula is C26H24N8O2 and the molecular weight is 480.52 g/mol. The chemical structure is as follows:

TUKYSA (tucatinib) is supplied as 50 mg and 150 mg film-coated tablets for oral use and contain the following inactive ingredients:

Tablet core: copovidone, crospovidone, sodium chloride, potassium chloride, sodium bicarbonate, colloidal silicon dioxide, magnesium stearate, and microcrystalline cellulose.

Coating: yellow film coat: polyvinyl alcohol, titanium dioxide, macrogol/polyethylene glycol, talc, and yellow iron oxide non-irradiated.

Each TUKYSA 50 mg tablet contains 10.10 mg (0.258 mEq) potassium and 9.21 mg (0.401 mEq) sodium.

Each TUKYSA 150 mg tablet contains 30.29 mg (0.775 mEq) potassium and 27.64 mg (1.202 mEq) sodium.

12 CLINICAL PHARMACOLOGY

12.1 Mechanism of Action

Tucatinib is a tyrosine kinase inhibitor of HER2. In vitro, tucatinib inhibits phosphorylation of HER2 and HER3, resulting in inhibition of downstream MAPK and AKT signaling and cell proliferation, and showed anti-tumor activity in HER2 expressing tumor cells. In vivo, tucatinib inhibited the growth of HER2 expressing tumors. The combination of tucatinib and trastuzumab showed increased anti-tumor activity in vitro and in vivo compared to either drug alone.

12.2 Pharmacodynamics

Exposure Response Relationship

Tucatinib exposure-response relationships and the time course of pharmacodynamics response have not been fully characterized.

Cardiac Electrophysiology

No large mean increase in QTc (i.e., > 20 ms) was detected following treatment with TUKYSA at the recommended dose of 300 mg taken orally twice daily.

12.3 Pharmacokinetics

Tucatinib AUC0-INF and Cmax increased proportionally over a dosage range from 50 mg to 300 mg (0.17 to 1 times the approved recommended dosage). Time to steady state was approximately 4 days. Steady-state pharmacokinetic parameters following administration of TUKYSA 300 mg twice daily for 7 days in patients with mBC and mCRC are described in Table 9. The geometric mean (CV%) tucatinib AUC accumulation ratios ranged from 2.0 (26) fold to 2.5 (28) fold.

Table 9: Tucatinib Cmax and AUC
Tumor Type | AUCss (ng*h/mL) | Cmax,ss (ng/mL) | Ctrough,ss (ng/mL)
mBC | 5620 (43) | 747 (45) | 288 (59)
mCRC | 3370 (49) | 405 (45) | 197 (63)

Absorption

The median time to peak plasma concentration of tucatinib was approximately 2 hours (range 1 to 4 hours).

Effects of Food

Following administration of a single oral dose of TUKYSA in 11 subjects after a high-fat meal (approximately 58% fat, 26% carbohydrate, and 16% protein), the mean AUC0-INF increased by 1.5-fold, the Tmax shifted from 1.5 hours to 4 hours, and Cmax was unaltered. The effect of food on the pharmacokinetics of tucatinib was not clinically meaningful.

Distribution

The geometric mean (CV%) apparent volume of distribution of tucatinib at steady-state were 903 (42) L and 829 (21) L in patients with mBC and mCRC, respectively. The plasma protein binding was 97.1% at clinically relevant concentrations.

At steady-state, concentrations of tucatinib and its metabolite ONT-993 in the cerebrospinal fluid were comparable to unbound plasma concentrations.

Elimination

At steady-state, tucatinib effective half-life was approximately 11.9 hours and geometric mean (CV%) apparent clearance was 53 (43) L/h in patients with mBC. Tucatinib effective half-life was approximately 16.4 hours and geometric mean (CV%) apparent clearance was 89 (49) L/h in patients with mCRC.

Metabolism

Tucatinib is metabolized primarily by CYP2C8 and to a lesser extent via CYP3A.

Excretion

Following a single oral dose of 300 mg radiolabeled tucatinib, approximately 86% of the total radiolabeled dose was recovered in feces (16% of the administered dose as unchanged tucatinib) and 4.1% in urine with an overall total recovery of 90% within 13 days post-dose. In plasma, approximately 76% of the plasma radioactivity was unchanged, 19% was attributed to identified metabolites, and approximately 5% was unassigned.

Specific Populations

Age (18-77 years), albumin (19 to 52 g/L), creatinine clearance (CLcr: 60 to 89 mL/min (n = 63); CLcr 30 to 59 mL/min (n = 6)), body weight (41 to 146 kg), sex (male (n = 170), female (n = 113)) and race (White (n = 205), Black (n = 37), or Asian (n = 25)) did not have a clinically meaningful effect on tucatinib exposure.

Renal Impairment

No clinically significant differences in the pharmacokinetics of tucatinib were observed in patients with mild to moderate renal impairment (CLcr: 30 to 89 mL/min by Cockcroft-Gault). The effect of severe renal impairment (CLcr: < 30 mL/min) on the pharmacokinetics of tucatinib is unknown.

Hepatic Impairment

Mild (Child-Pugh A) and moderate (Child-Pugh B) hepatic impairment had no clinically relevant effect on tucatinib exposure. Tucatinib AUC0-INF was increased by 1.6 fold in subjects with severe (Child-Pugh C) hepatic impairment compared to subjects with normal hepatic function.

Drug Interaction Studies

Clinical Studies

Table 10: Effect of Other Drugs on TUKYSA
Concomitant Drug (Dose) | TUKYSA Dose | Ratio (90% CI) of Tucatinib Exposure With and Without Concomitant Drug
Concomitant Drug (Dose) | TUKYSA Dose | Cmax | AUC
Strong CYP3A Inhibitor Itraconazole (200 mg BID) | 300 mg single dose | 1.3 (1.2, 1.4) | 1.3 (1.3, 1.4)
Strong CYP3A/Moderate 2C8 Inducer Rifampin (600 mg once daily) | 300 mg single dose | 0.6 (0.5, 0.8) | 0.5 (0.4, 0.6)
Strong CYP2C8 Inhibitor Gemfibrozil (600 mg BID) | 300 mg single dose | 1.6 (1.5, 1.8) | 3.0 (2.7, 3.5)

Table 11: Effect of TUKYSA on Other Drugs
Concomitant Drug (Dose) | TUKYSA Dose | Ratio (90% CI) of Exposure Measures of Concomitant Drug with/without Tucatinib
Concomitant Drug (Dose) | TUKYSA Dose | Cmax | AUC
CYP2C8 Substrate Repaglinide (0.5 mg single dose) | 300 mg twice daily | 1.7 (1.4, 2.1) | 1.7 (1.5, 1.9)
CYP3A Substrate Midazolam (2 mg single dose) | 300 mg twice daily | 3.0 (2.6, 3.4) | 5.7 (5.0, 6.5)
P-gp Substrate Digoxin (0.5 mg single dose) | 300 mg twice daily | 2.4 (1.9, 2.9) | 1.5 (1.3, 1.7)
MATE1/2-K substrate [Tucatinib reduced the renal clearance of metformin without any effect on glomerular filtration rate (GFR) as measured by iohexol clearance and serum cystatin C.] Metformin (850 mg single dose) | 300 mg twice daily | 1.1 (1.0, 1.2) | 1.4 (1.2, 1.5)

No clinically significant difference in the pharmacokinetics of tucatinib were observed when used concomitantly with omeprazole (proton pump inhibitor) or tolbutamide (sensitive CYP2C9 substrate).

In Vitro Studies

Cytochrome P450 (CYP) Enzymes: Tucatinib is a reversible inhibitor of CYP2C8 and CYP3A and a time-dependent inhibitor of CYP3A, but is not an inhibitor of CYP1A2, CYP2B6, CYP2C9, CYP2C19, or CYP2D6.

Uridine diphosphate (UDP)-glucuronosyl transferase (UGT) Enzymes: Tucatinib is not an inhibitor of UGT1A1.

Transporter Systems: Tucatinib is a substrate of P-gp and BCRP, but is not a substrate of OAT1, OAT3, OCT1, OCT2, OATP1B1, OATP1B3, MATE1, MATE2-K, or BSEP.

Tucatinib inhibits MATE1/MATE2-K-mediated transport of metformin and OCT2/MATE1-mediated transport of creatinine. The observed serum creatinine increase in clinical studies with tucatinib is due to inhibition of tubular secretion of creatinine via OCT2 and MATE1.

13 NONCLINICAL TOXICOLOGY

13.1 Carcinogenesis, Mutagenesis, Impairment of Fertility

Carcinogenicity studies have not been conducted with tucatinib.

Tucatinib was not mutagenic in an in vitro bacterial reverse mutation (Ames) assay. Tucatinib was not clastogenic in either an in vitro chromosome aberration assay or an in vivo mouse bone marrow micronucleus assay.

Fertility studies in animals have not been conducted. In repeat-dose toxicity studies up to 13 weeks duration, decreased corpora lutea/corpus luteum cyst, increased interstitial cells of the ovary, atrophy of the uterus, and mucification of the vagina were observed in female rats at doses ≥ 6 mg/kg/day (approximately 0.1 times the human exposure at the recommended dose based on AUC). Atrophy and edema of the testes and oligospermia/germ cell debris in the epididymides were observed in male rats at ≥ 120 mg/kg/day (approximately 13 times the human exposure at the recommended dose based on AUC).

14 CLINICAL STUDIES

14.1 HER2-Positive Metastatic Breast Cancer

The efficacy of TUKYSA in combination with trastuzumab and capecitabine was evaluated in 612 patients in HER2CLIMB (NCT02614794), a randomized (2:1), double-blind, placebo-controlled trial. Patients were required to have HER2-positive, unresectable locally advanced or metastatic breast cancer, with or without brain metastases, and prior treatment with trastuzumab, pertuzumab, and ado-trastuzumab emtansine (T-DM1) separately or in combination, in the neoadjuvant, adjuvant or metastatic setting. HER2 positivity was based on archival or fresh tissue tested with an FDA-approved test at a central laboratory prior to enrollment with HER2 positivity defined as HER2 IHC 3+ or ISH positive.

Patients with brain metastases, including those with progressing or untreated lesions, were eligible provided they were neurologically stable and did not require immediate radiation or surgery. The trial excluded patients with leptomeningeal disease. Randomization was stratified by the presence or history of brain metastases (yes vs. no), Eastern Cooperative Oncology Group (ECOG) performance status (0 vs. 1), and region (U.S., Canada, or rest of world).

Patients received TUKYSA 300 mg or placebo orally twice daily with a trastuzumab or a non-US approved trastuzumab product loading dose of 8 mg/kg on Day 1 of Cycle 1 if needed and then a maintenance dose of 6 mg/kg on Day 1 of every 21-day cycle thereafter and capecitabine 1000 mg/m^2 orally twice daily on Days 1 through 14 of every 21-day cycle. An alternate trastuzumab dosing regimen was 600 mg administered subcutaneously on Day 1 of every 21-day cycle. Patients were treated until disease progression or unacceptable toxicity. Tumor assessments, including brain-MRI in patients with presence or history of brain metastases at baseline, occurred every 6 weeks for the first 24 weeks and every 9 weeks thereafter.

The major efficacy outcome measure was progression-free survival (PFS) in the first 480 randomized patients assessed by blinded independent central review (BICR) using Response Evaluation Criteria in Solid Tumors (RECIST) v1.1. Additional efficacy outcome measures were evaluated in all randomized patients and included overall survival (OS), PFS among patients with a history or presence of brain metastases (PFSBrainMets), and confirmed objective response rate (ORR).

The median age was 54 years (range: 22 - 82); 116 (19%) patients were age 65 or older. The majority were White (73%) and female (99%) and 51% had an ECOG performance status of 1. Sixty percent had estrogen and/or progesterone receptor-positive disease. Forty-eight percent had a presence or history of brain metastases; of these patients, 23% had untreated brain metastases, 40% had treated but stable brain metastases, and 37% had treated but radiographically progressing brain metastases. Seventy-four percent of patients had visceral metastases. Patients had received a median of 4 (range, 2 to 17) prior lines of systemic therapy and a median of 3 (range, 1 to 14) prior lines of systemic therapy in the metastatic setting. All patients received prior trastuzumab and T-DM1 and all but two patients had prior pertuzumab.

Efficacy results are summarized in Table 12 and Figure 1 and 2. Efficacy results were consistent across patient subgroups defined by stratification factors (presence or history of brain metastases, ECOG status, region of world) and hormone receptor status.

Table 12: Efficacy Results in HER2CLIMB
 | TUKYSA + Trastuzumab + Capecitabine | Placebo + Trastuzumab + Capecitabine
PFS [Primary PFS analysis conducted in first 480 randomized patients.] | N=320 | N=160
Number of events (%) | 178 (56) | 97 (61)
Median, months (95% CI) | 7.8 (7.5, 9.6) | 5.6 (4.2, 7.1)
Hazard ratio (95% CI) [Hazard ratio and 95% confidence intervals are based on stratified Cox proportional hazards regression model controlling for stratification factors (presence or history of brain metastases, ECOG status, and region of world)] | 0.54 (0.42, 0.71)
P-value [Two-sided p-value based on re-randomization procedure (Rosenberger and Lachin 2002) controlling for stratification factors, compared with the allocated alpha of 0.05] | <0.00001
OS | N=410 | N=202
Number of deaths (%) | 130 (32) | 85 (42)
Median, months (95% CI) | 21.9 (18.3, 31.0) | 17.4 (13.6, 19.9)
Hazard ratio (95% CI) | 0.66 (0.50, 0.87)
P-value [Two-sided p-value based on re-randomization procedure (Rosenberger and Lachin 2002) controlling for stratification factors, compared with the allocated alpha of 0.0074 for this interim analysis (with 60% of the planned number of events for final analysis)] | 0.00480
PFSBrainMets [Analysis includes patients with history or presence of parenchymal brain metastases at baseline, including target and non-target lesions. Does not include patients with dural lesions only.] | N=198 | N=93
Number of events (%) | 106 (53.5) | 51 (54.8)
Median, months (95% CI) | 7.6 (6.2, 9.5) | 5.4 (4.1, 5.7)
Hazard ratio (95% CI) | 0.48 (0.34, 0.69)
P-value [Two-sided p-value based on re-randomization procedure (Rosenberger and Lachin 2002) controlling for stratification factors, compared with the allocated alpha of 0.0080 for this interim analysis (with 71% of the planned number of events for final analysis)] | <0.00001
Confirmed ORR for Patients with Measurable Disease | N=340 | N=171
ORR (95% CI) [Two-sided 95% exact confidence interval, computed using the Clopper-Pearson method (1934)] | 40.6 (35.3, 46.0) | 22.8 (16.7, 29.8)
CR (%) | 3 (0.9) | 2 (1.2)
PR (%) | 135 (39.7) | 37 (21.6)
P-value | 0.00008
DOR
Median, months (95% CI) [Calculated using the complementary log-log transformation method (Collett, 1994)] | 8.3 (6.2, 9.7) | 6.3 (5.8, 8.9)
BICR=blinded independent central review; CI=confidence interval; PFS=progression-free survival; OS=overall survival; ORR=objective response rate; CR=complete response; PR=partial response; DOR=duration of response.

14.2 HER2-Positive Metastatic Colorectal Cancer

The efficacy of TUKYSA in combination with trastuzumab was evaluated in 84 patients in MOUNTAINEER (NCT03043313), an open-label, multicenter trial. Patients were required to have HER2-positive, RAS wild-type, unresectable or metastatic colorectal cancer and prior treatment with fluoropyrimidines, oxaliplatin, irinotecan, and anti-vascular endothelial growth factor (VEGF) monoclonal antibody (mAb). Patients whose disease had deficient mismatch repair (dMMR) proteins or microsatellite instability-high (MSI-H) must have also received an anti-programmed cell death protein-1 (PD-1) mAb. Patients who received prior anti-HER2 targeting therapy were excluded. HER2 positivity as defined by HER2 overexpression or gene amplification was prospectively determined in local laboratories using immunohistochemistry (IHC), in situ hybridization (ISH), and/or next generation sequencing (NGS) on tumor tissue. RAS status was performed as standard of care prior to study entry based on expanded RAS testing including KRAS exons 2, 3, and 4 and NRAS exons 2, 3, and 4.

The median age was 55 years (range: 24 to 77); 12 (14%) patients were age 65 or older. Seventy-seven percent of patients were White, 4% were Black, 4% were Asian, and 4% were Hispanic or Latino. Sixty-one percent of patients were male. Seventy percent of patients had lung metastases, 64% had liver metastases, 60% had an ECOG performance status of 0, 37% had an ECOG performance status of 1, and 4% had an ECOG performance status of 2. Ninety-nine percent of patients received prior treatment with fluoropyrimidine, oxaliplatin, and irinotecan and 83% and 52% received anti-VEGF antibodies and anti-EGFR antibodies respectively; 23%, 38%, and 39% received 1, 2, or ≥3 prior lines of therapy, respectively.

Patients received TUKYSA 300 mg orally twice per day with a loading dose of trastuzumab or a non-US approved trastuzumab product 8 mg/kg intravenously on Day 1 of Cycle 1, followed by a maintenance dose of trastuzumab 6 mg/kg on Day 1 of each subsequent 21-day cycle. Patients were treated until disease progression or unacceptable toxicity.

The major efficacy outcome measures were overall response rate (ORR) and duration of response (DOR) as assessed by blinded independent central review (BICR) according to RECIST version 1.1.

Efficacy results are summarized in Table 13.

Table 13: Efficacy Results in MOUNTAINEER
 | TUKYSA + trastuzumab N=84
Overall Response Rate (%) (95% CI) | 38 (28, 49)
CR (%) | 3 (3.6)
PR (%) | 29 (35)
Duration of Response | N=32
Median [Based on Kaplan-Meier method.] , months (95% CI) | 12.4 (8.5, 20.5)
Patients with DOR≥6 months [Based on observed duration of response.] | 81%
Patients with DOR≥12 months | 34%

16 HOW SUPPLIED/STORAGE AND HANDLING

16.1 How Supplied

TUKYSA 50 mg tablets are supplied as yellow, film-coated, round tablets containing 50 mg of tucatinib. Each tablet is debossed with “TUC” on one side and “50” on the other side, and is packaged as follows:

50 mg tablets: 60 count in 75 cc bottle: NDC 51144-001-60

TUKYSA 150 mg tablets are supplied as yellow, film-coated, oval-shaped tablets containing 150 mg of tucatinib. Each tablet is debossed with “TUC” on one side and “150” on the other side, and is packaged as follows:

150 mg tablets: 60 count in 75 cc bottle: NDC 51144-002-60

150 mg tablets: 120 count in 150 cc bottle: NDC 51144-002-12

Store at controlled room temperature, 20ºC to 25ºC (68ºF to 77ºF); excursions permitted from 15ºC to 30ºC (59ºF to 86ºF) [see USP Controlled Room Temperature].

Dispense to patient in original container only. Store in original container to protect from moisture. Replace cap securely each time after opening. Do not discard desiccant.

Once opened, use within 3 months. Discard any unused tablets 3 months after opening the bottle.

17 PATIENT COUNSELING INFORMATION

Advise the patient to read the FDA-approved patient labeling (Patient Information).

Diarrhea

- Inform patients that TUKYSA has been associated with severe diarrhea. Instruct patients on how to manage diarrhea and to inform their healthcare provider immediately if there is any change in bowel patterns [see Warnings and Precautions (5.1)].

Hepatotoxicity

- Inform patients that TUKYSA has been associated with severe hepatotoxicity and that they should report signs and symptoms of liver dysfunction to their healthcare provider immediately [see Warnings and Precautions (5.2)].

Embryo-Fetal Toxicity

- Inform pregnant women and females of reproductive potential of the risk to a fetus. Advise females to inform their healthcare provider of a known or suspected pregnancy [see Warnings and Precautions (5.3) and Use in Specific Populations (8.1)].
- Advise females of reproductive potential to use effective contraception during treatment with TUKYSA and for 1 week after the last dose [see Use in Specific Populations (8.3)].
- Advise male patients with female partners of reproductive potential to use effective contraception during treatment with TUKYSA and for 1 week after the last dose [see Use in Specific Populations (8.3)].
- Refer to the Full Prescribing Information of trastuzumab and capecitabine for pregnancy and contraception information.

Lactation

- Advise women not to breastfeed during treatment with TUKYSA and for 1 week after the last dose [see Use in Specific Populations (8.2)]. Refer to the Full Prescribing Information of trastuzumab and capecitabine for lactation information.

Infertility

- Advise males and females of reproductive potential that TUKYSA may impair fertility [see Use in Specific Populations (8.3)]. Refer to the Full Prescribing Information of trastuzumab and capecitabine for infertility information.

Manufactured for:
Seagen Inc.
Bothell, WA 98021
1-855-4SEAGEN

TUKYSA, Seagen, and are US registered trademarks of Seagen Inc.
© 2023 Seagen Inc., Bothell, WA 98021. All rights reserved.
USPI-213411-v04

PATIENT INFORMATION
TUKYSA® (too-KYE-sah)
(tucatinib)
tablets

Important information: If your healthcare provider prescribes TUKYSA in combination with capecitabine for your breast cancer, also read the Patient Information that comes with capecitabine.

What is TUKYSA?
TUKYSA is a prescription medicine used to treat adults with:

- a type of breast cancer called human epidermal growth factor receptor-2 (HER2)-positive breast cancer. TUKYSA is used with the medicines trastuzumab and capecitabine, when your cancer has spread to other parts of the body such as the brain (metastatic), or cannot be removed by surgery, and you have received one or more anti-HER2 breast cancer treatments.
- a type of colorectal cancer called RAS wild-type HER2-positive colorectal cancer. TUKYSA is used with the medicine trastuzumab, when your cancer has spread to other parts of the body (metastatic), or cannot be removed by surgery, and you have received treatment with fluoropyrimidine-, oxaliplatin-, and irinotecan-based chemotherapy and it did not work or is no longer working.

It is not known if TUKYSA is safe and effective in children.

Before taking TUKYSA, tell your healthcare provider about all of your medical conditions, including if you:

- have liver problems.
- are pregnant or plan to become pregnant. TUKYSA can harm your unborn baby.
  Females who are able to become pregnant:
  - Your healthcare provider will do a pregnancy test before you start treatment with TUKYSA.
  - You should use effective birth control (contraception) during treatment with TUKYSA and for 1 week after the last dose of TUKYSA. Talk with your healthcare provider about forms of birth control that you can use during this time.
  - Tell your healthcare provider right away if you become pregnant or think you may be pregnant during treatment with TUKYSA.
Males with female partner who are able to become pregnant should use effective birth control during treatment with TUKYSA and for 1 week after the last dose of TUKYSA.
- are breastfeeding or plan to breastfeed. It is not known if TUKYSA passes into your breast milk. Do not breastfeed during treatment with TUKYSA and for 1 week after the last dose of TUKYSA.

Tell your healthcare provider about all the medicines you take, including prescription and over-the-counter medicines, vitamins, and herbal supplements. TUKYSA may affect the way your other medicines work, and other medicines may affect the way TUKYSA works.

Know the medicines you take. Keep a list of all the medicines you take and show it to your healthcare provider and pharmacist every time you get a new medicine.

How should I take TUKYSA?

- Take TUKYSA exactly as your healthcare provider tells you.
- TUKYSA is used with the medicine trastuzumab for colorectal cancer or with trastuzumab and capecitabine for breast cancer. Your healthcare provider will tell you the dose of trastuzumab and capecitabine you will take and how you will receive them.
- Take TUKYSA 2 times a day, with or without a meal.
- Take TUKYSA about 12 hours apart or at the same times every day.
- Swallow TUKYSA tablets whole. Do not chew, crush, or split TUKYSA tablets before swallowing. Do not take TUKYSA tablets if they are broken, cracked, or damaged.
- If you vomit or miss a dose of TUKYSA, take your next dose at your regular time.

What are the possible side effects of TUKYSA?
TUKYSA may cause serious side effects, including:

- Diarrhea. Diarrhea is common with TUKYSA and can sometimes be severe. Tell your healthcare provider if you have a change in your bowel movements or severe diarrhea. Severe diarrhea can lead to loss of too much body fluids (dehydration), low blood pressure, kidney problems and death. Your healthcare provider may prescribe medicines to treat your diarrhea during treatment with TUKYSA.
- Liver Problems. TUKYSA can cause severe liver problems. Your healthcare provider will do blood tests to check your liver function before and every 3 weeks during treatment with TUKYSA, or as needed. Tell your healthcare provider right away if you have any signs and symptoms of liver problems including:

- itching
- yellowing of your skin or eyes
- dark or brown urine (tea-colored)
- pain in the upper right side of your stomach-area (abdomen)

- feel very tired
- decreased appetite
- bleeding or bruising more easily than normal

The most common side effects of TUKYSA in combination with trastuzumab and capecitabine in adults with HER2-positive breast cancer include:

- diarrhea
- rash, redness, pain, swelling or blisters on the palms of your hands or soles of your feet
- nausea
- increased liver function blood tests
- vomiting

- mouth sores (stomatitis)
- decreased appetite
- low red blood cell counts (anemia)
- rash

The most common side effects of TUKYSA in combination with trastuzumab in adults with RAS wild-type HER2-positive colorectal cancer include:

- diarrhea
- tiredness
- rash

- nausea
- stomach-area (abdomen) pain
- infusion-related reactions
- fever

Your healthcare provider may change your dose of TUKYSA, temporarily stop, or permanently stop treatment with TUKYSA if you have certain side effects.
TUKYSA may cause fertility problems in males and females, which may affect the ability to have children. Talk to your healthcare provider if you have concerns about fertility. These are not all of the possible side effects of TUKYSA. Call your doctor for medical advice about side effects. You may report side effects to FDA at 1-800-FDA-1088.

How should I store TUKYSA?

- Store TUKYSA at room temperature 68°F to 77°F (20ºC to 25ºC).
- Keep TUKYSA in its original container. The TUKYSA bottle contains a desiccant packet to help keep your tablets dry (protect from moisture). Keep the desiccant in the bottle.
- Tightly close the bottle of TUKYSA after you take your dose.
- TUKYSA must be used within 3 months after opening the bottle. Throw away (discard) any unused tablets 3 months after opening the bottle.

Keep TUKYSA and all medicines out of reach of children.

General information about the safe and effective use of TUKYSA.
Medicines are sometimes prescribed for conditions not listed in the Patient Information. Do not use TUKYSA for a condition for which it was not prescribed. Do not give TUKYSA to other people, even if they have the same symptoms that you have. It may harm them. You can ask your pharmacist or healthcare provider for information about TUKYSA that is written for healthcare professionals.

What are the ingredients in TUKYSA?
Active ingredient: tucatinib
Inactive ingredients:
Tablet core: copovidone, crospovidone, sodium chloride, potassium chloride, sodium bicarbonate, colloidal silicon dioxide, magnesium stearate, and microcrystalline cellulose.

Tablet coating: yellow film coat: polyvinyl alcohol, titanium dioxide, macrogol/polyethylene glycol, talc, and yellow iron oxide non-irradiated.
Manufactured for: Seagen Inc., Bothell, WA 98021
TUKYSA is a registered trademark owned by Seagen Inc.
©2023 Seagen Inc.
PPI-213411-v04
For more information, call 1-855-473-2436 (1-855-4SEAGEN) or go to www.TUKYSA.com.

This Patient Information has been approved by the U.S. Food and Drug Administration. Revised: 01/2023

PRINCIPAL DISPLAY PANEL

NDC 51144-001-60
Rx Only
TUKYSA®
(tucatinib) tablets
50 mg*
Attention: Dispense and store Tukysa
in original container to protect from moisture.
Seagen®
60 Tablets
* Each tablet contains 50 mg tucatinib.
Recommended Dosage: See prescribing information
Store at controlled room temperature,
20°C to 25°C (68° to 77°F); excursions
permitted from 15°C to 30°C (59°F to 86°F)
[see USP Controlled Room Temperature].
KEEP OUT OF REACH OF CHILDREN
Discard unused tablets 3 months after opening.
Mfg for: Seagen Inc.
Bothell, WA 98021 USA
TUKYSA and its logo are US registered
trademarks of Seagen Inc.
©2023 Seagen Inc.
All rights reserved. Printed in USA
00000000
GTIN 00351144001607
LOT: 123456
EXP: MMMYYYY
SN: 12345678901234

NDC 51144-002-60
Rx Only
TUKYSA®
(tucatinib) tablets
150 mg*
Attention: Dispense and store Tukysa
in original container to protect from moisture.
Seagen®
60 Tablets
* Each tablet contains 150 mg tucatinib.
Recommended Dosage: See prescribing information
Store at controlled room temperature,
20°C to 25°C (68° to 77°F); excursions
permitted from 15°C to 30°C (59°F to 86°F)
[see USP Controlled Room Temperature].
KEEP OUT OF REACH OF CHILDREN
Discard unused tablets 3 months after opening.
Mfg for: Seagen Inc.
Bothell, WA 98021 USA
TUKYSA and its logo are US registered
trademarks of Seagen Inc.
©2023 Seagen Inc.
All rights reserved. Printed in USA
00000000
GTIN 00351144002604
LOT: 123456
EXP: MMMYYYY
SN: 12345678901234

NDC 51144-002-12
Rx Only
TUKYSA®
(tucatinib) tablets
150 mg*
Attention: Dispense and store Tukysa
in original container to protect from moisture.
SeaGen®
120 Tablets
* Each tablet contains 150 mg tucatinib.
Recommended Dosage: See prescribing information
Store at controlled room temperature, 20°C to 25°C
(68° to 77°F); excursions permitted from 15°C to 30°C
(59°F to 86°F) [see USP Controlled Room Temperature].
KEEP OUT OF REACH OF CHILDREN
Discard unused tablets 3 months after opening.
Mfg for: Seagen Inc.
Bothell, WA 98021 USA
TUKYSA and its logo are US registered trademarks of Seagen Inc.
©2021 Seagen Inc.
All rights reserved. Printed in USA
1204-02
GTIN 00351144002604
LOT: 123456
EXP: MMMYYYY
SN: 12345678901234